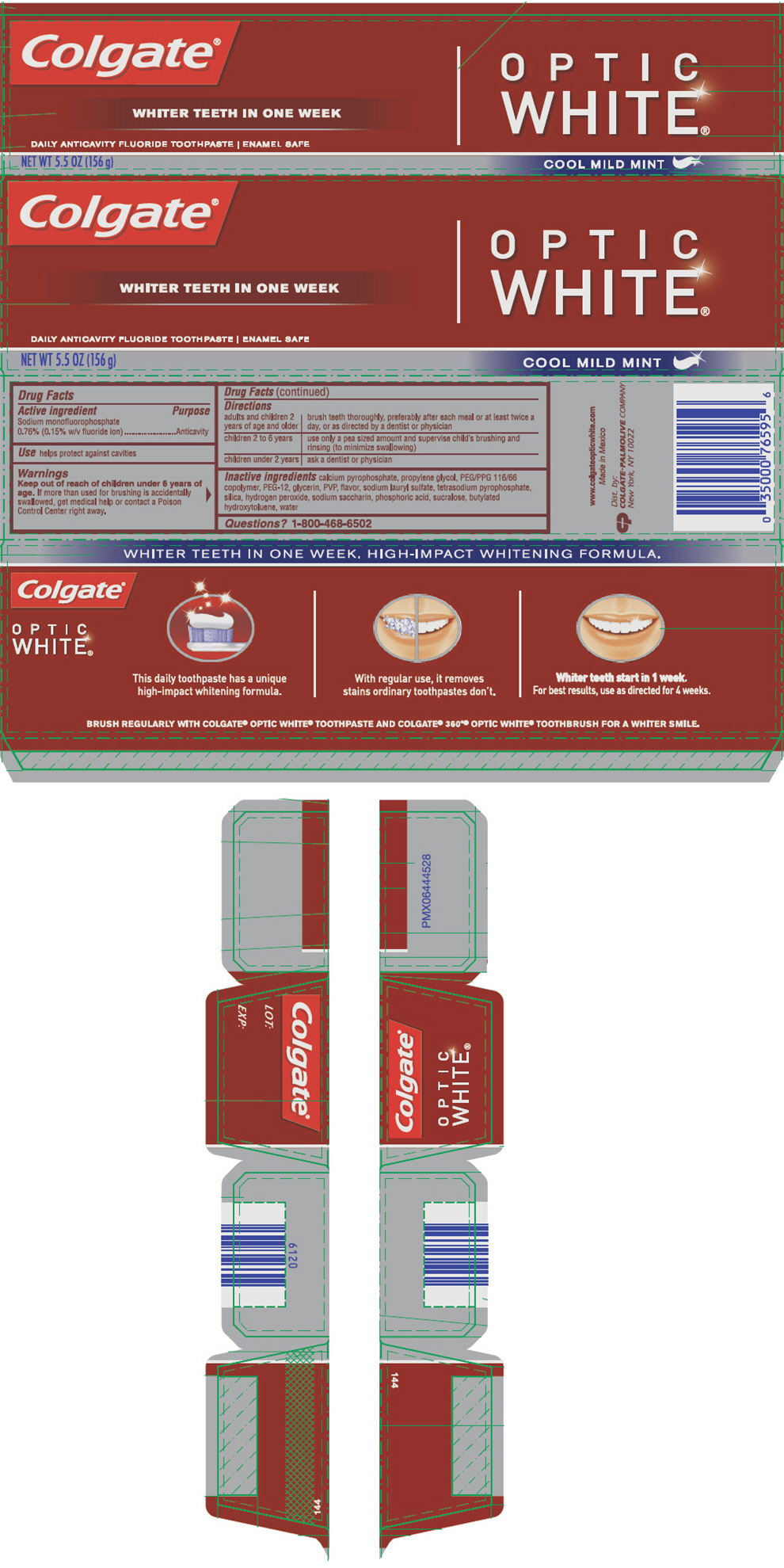 DRUG LABEL: Colgate Optic White 
NDC: 65954-560 | Form: PASTE, DENTIFRICE
Manufacturer: Mission Hills S.A de C.V
Category: otc | Type: HUMAN OTC DRUG LABEL
Date: 20130130

ACTIVE INGREDIENTS: SODIUM MONOFLUOROPHOSPHATE 1 mg/1 g
INACTIVE INGREDIENTS: CALCIUM PYROPHOSPHATE 351.1 mg/1 g; PROPYLENE GLYCOL; PEG/PPG-116/66 COPOLYMER; POLYETHYLENE GLYCOL 600; GLYCERIN; POVIDONE K15; SODIUM LAURYL SULFATE; SODIUM PYROPHOSPHATE; SILICON DIOXIDE; HYDROGEN PEROXIDE; SACCHARIN SODIUM; PHOSPHORIC ACID; SUCRALOSE; BUTYLATED HYDROXYTOLUENE; WATER

Colgate® Optic White® Cool Mild Mint Fluoride Toothpaste 5.5OZ

Drug Facts

Active ingredient

Sodium monofluorophosphate 0.76% (0.15% w/v fluoride ion)

Purpose

Anticavity

Use

helps protect against cavities

Warnings

Keep out of reach of children under 6 years of age. If more than used for brushing is accidentally swallowed, get medical help or contact a Poison Control Center right away.

Directions

adults and children 2 years of age and older | brush teeth thoroughly, preferably after each meal or at least twice a day, or as directed by a dentist or physician
children 2 to 6 years | use only a pea sized amount and supervise child's brushing and rinsing (to minimize swallowing)
children under 2 years | as a dentist or physician

Inactive ingredients

calcium pyrophosphate, propylene glycol, PEG/PPG 116/66 copolymer, PEG-12, glycerin, PVP, flavor, sodium lauryl sulfate, tetrasodium pyrophosphate, silica, hydrogen peroxide, sodium saccharin, phosphoric acid, sucralose, butylated hydroxytoluene, water

Questions?

1-800-468-6502

Dist. by:
COLGATE-PALMOLIVE COMPANY
New York, NY 10022

PRINCIPAL DISPLAY PANEL - 156 g Tube Carton Label

Colgate®

WHITER TEETH IN ONE WEEK

OPTIC
WHITE®

DAILY ANTICAVITY FLUORIDE TOOTHPASTE | ENAMEL SAFE

NET WT 5.5 OZ (156 g)
COOL MILD MINT